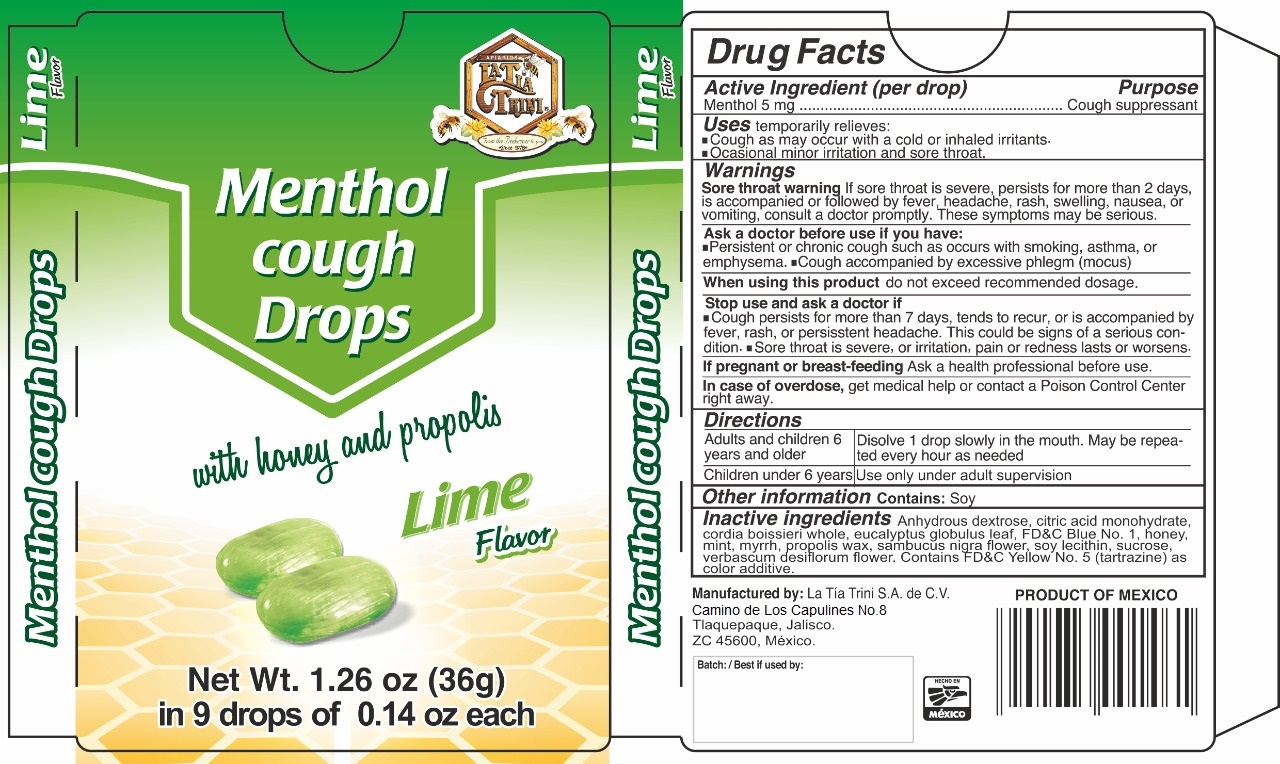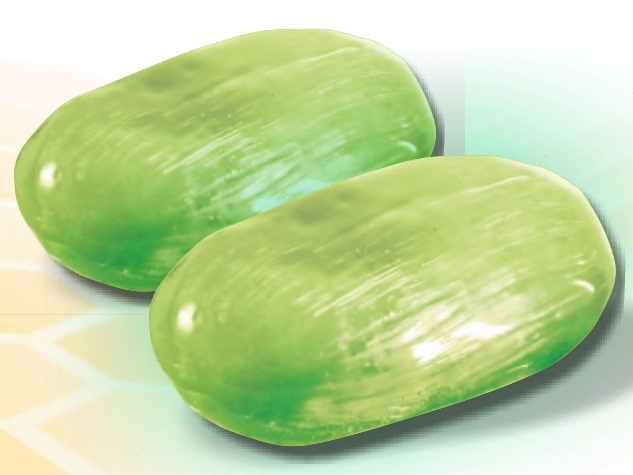 DRUG LABEL: Menthol Cough Drops
NDC: 72432-200 | Form: PASTILLE
Manufacturer: LA TIA TRINI SA DE CV
Category: otc | Type: HUMAN OTC DRUG LABEL
Date: 20210729

ACTIVE INGREDIENTS: MENTHOL 0.005 g/4 g
INACTIVE INGREDIENTS: CITRIC ACID MONOHYDRATE; EUCALYPTUS GLOBULUS LEAF; ANHYDROUS DEXTROSE; SAMBUCUS NIGRA FLOWER; MYRRH; MINT; PROPOLIS WAX; HONEY; FD&C BLUE NO. 1; VERBASCUM DENSIFLORUM FLOWER; CORDIA BOISSIERI WHOLE; SUCROSE; LECITHIN, SOYBEAN; FD&C YELLOW NO. 5

Menthol Cough Drops

Menthol Cough Drops

Menthol 5 mg Purpose: Cough suppressant.

Purpose

Cough suppressant

Uses

Temporarily relieves:

- Cough as may occur with a cold or inhaled irritants.
- Ocasional minor irritation and sore throat.

Warnings

Sore throat warning if sore throat is severe, persists, for more than 2 days, is accompained or followed by fever, headache, rash, swelling, nausea, or vomiting, consult a doctor promptly. This symptoms may be serious.

Ask a doctor before use if you have:

• Persistent or chronic cough such as occurs with smoking, asthma, or emphysema. • Cough accompained by excessive phlegm (mocus).

When using this product

Do not exceed recommended dosage.

Stop use and ask a doctor if

Cough persists for more than 7 days, tends to recur, or is accompained by fever, rash, or persisstent headache. This could be signs of a serious condition.

Sore throat is severe, or irritation, pain or redness lasts or worsens.

If pregmant or breast-feeding Ask a health professional before use.

In case of overdose, get medical help or contact a Poison Control Center right away.

Directions

- Adults and children 6 years and older: Disolve 1 drop slowly in the mouth. May be repeated every hour as needed.
- Children under 6 years: Use only under adult supervision.

Other information

Contains: Soy

Inactive Ingredients

Anhydrous dextrose, citric acid monohydrate, cordia boissieri whole, eucalyptus globulus leaf, FD&C Blue No.1, honey, mint, myrrh, propolis wax, sambucus nigra flower, soy lecithin, sucrose, verbascum densiflorum flower. Contains FD&C Yellow No. 5 (tartrazine) as a color additive.

Package Label - Menthol Drops

MentholDrops NDC: 72432-200-01